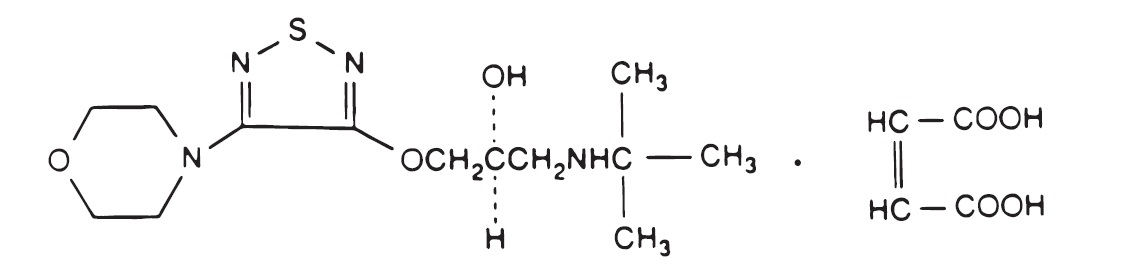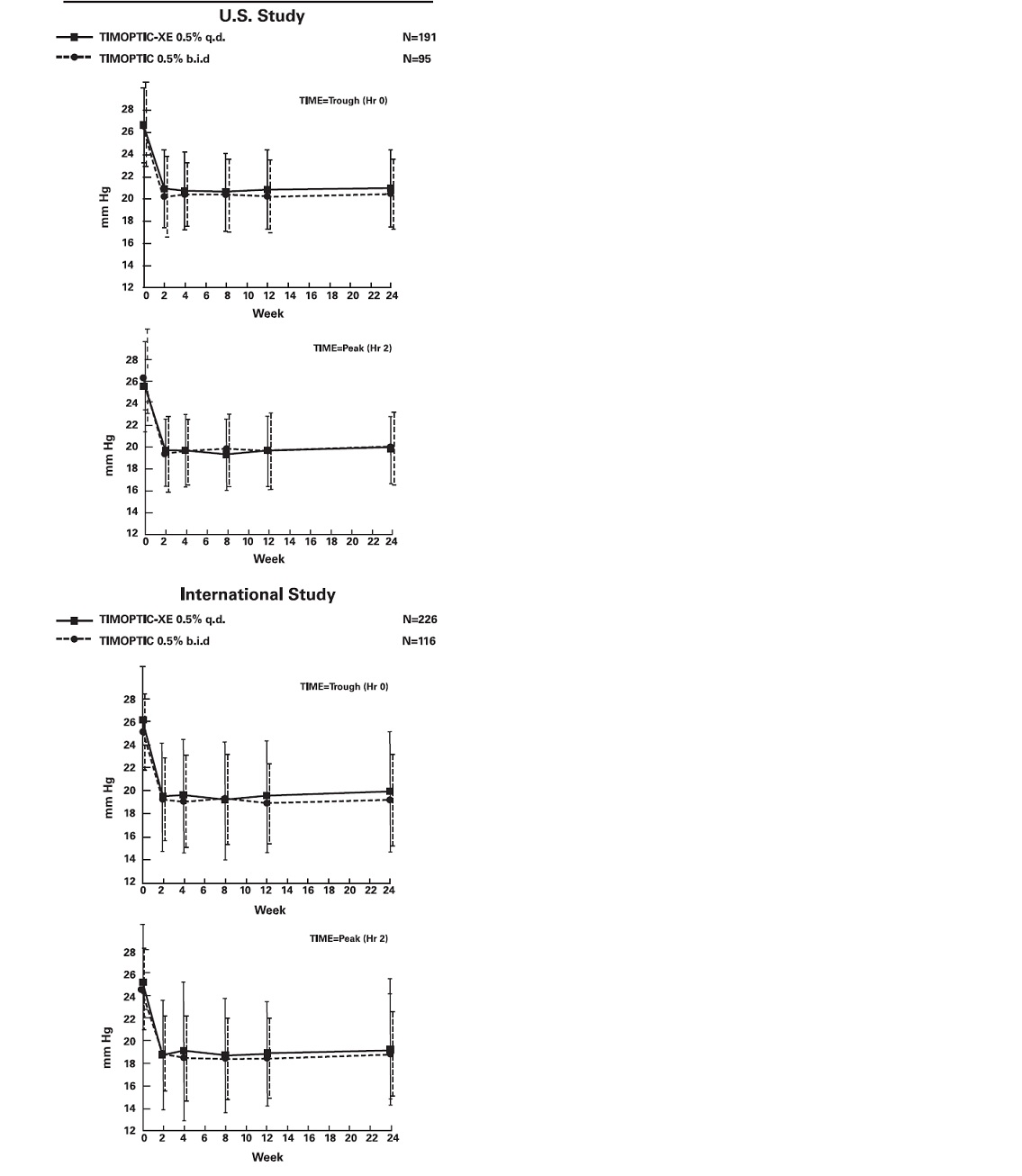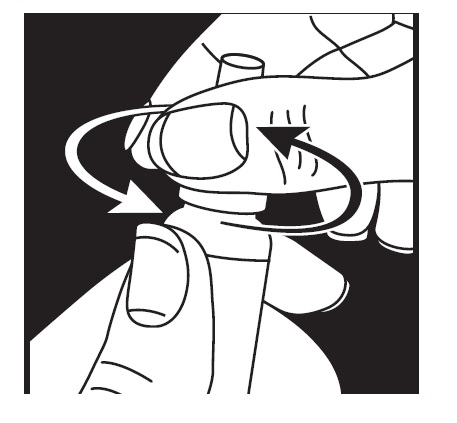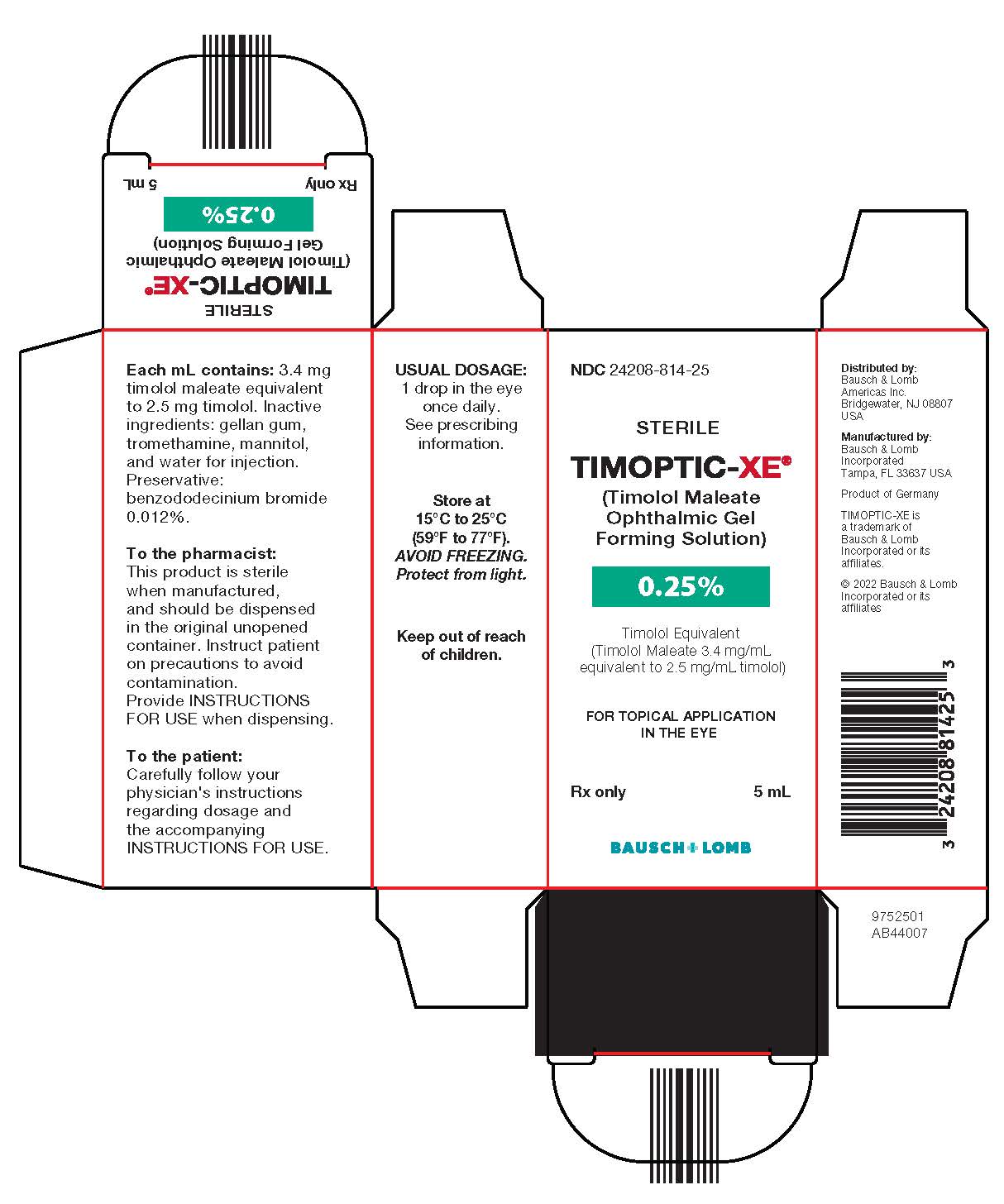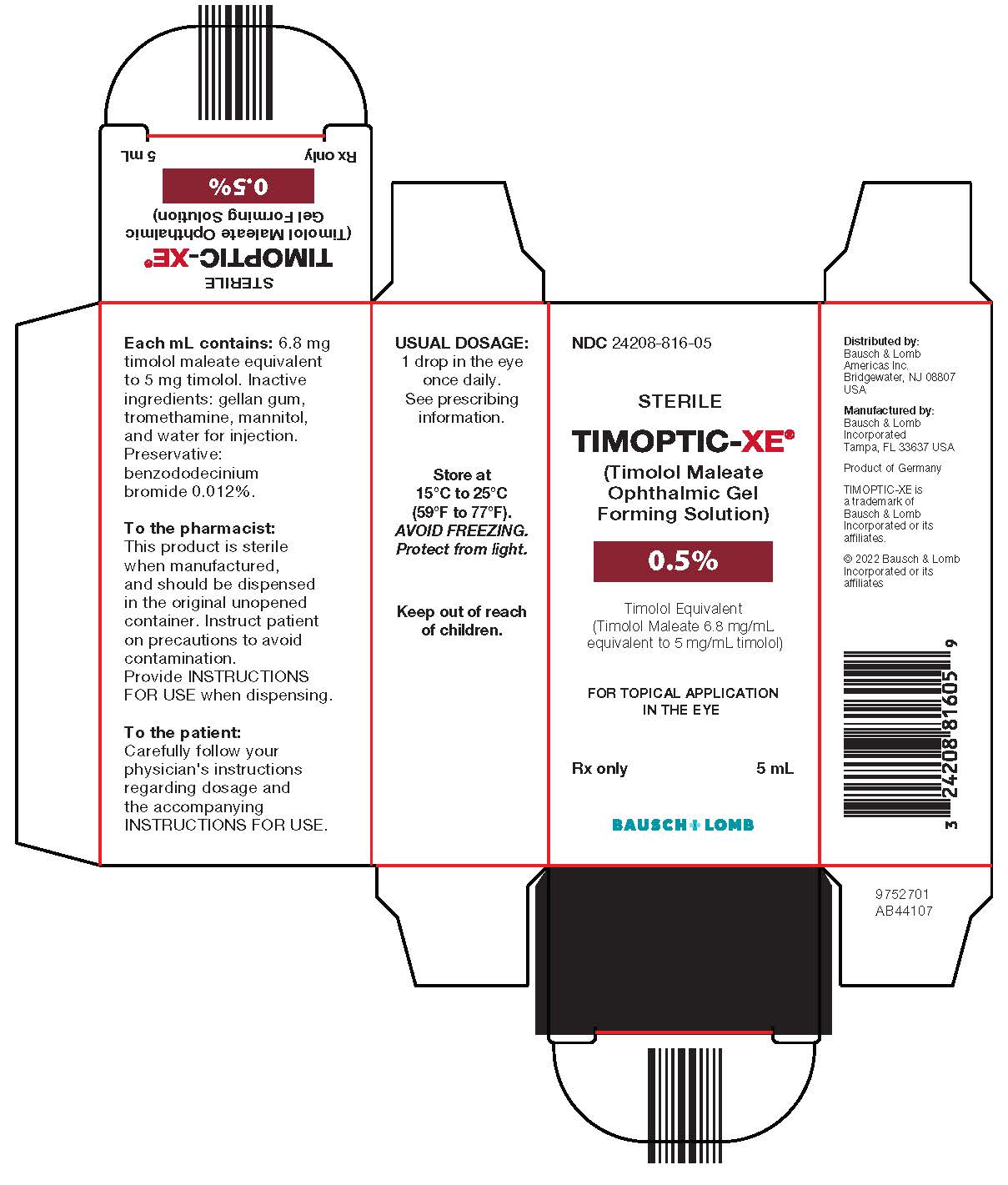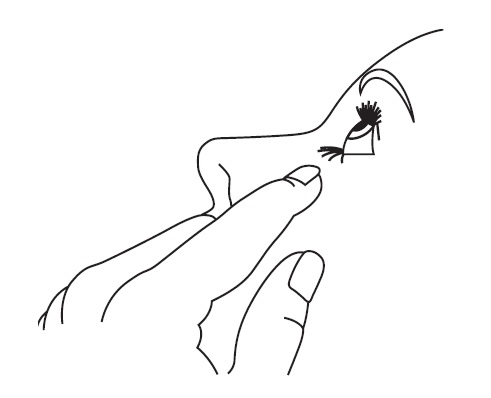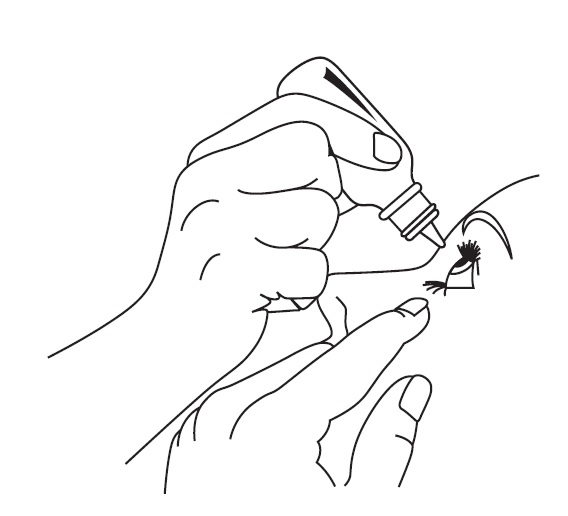 DRUG LABEL: Timoptic-XE
NDC: 24208-814 | Form: SOLUTION
Manufacturer: Bausch & Lomb Incorporated
Category: prescription | Type: HUMAN PRESCRIPTION DRUG LABEL
Date: 20220331

ACTIVE INGREDIENTS: Timolol Maleate 2.5 mg/1 mL
INACTIVE INGREDIENTS: Tromethamine; Mannitol; Water; Benzododecinium Bromide

STERILE OPHTHALMIC GEL FORMING SOLUTION
TIMOPTIC-XE® 0.25% AND 0.5%
(TIMOLOL MALEATE OPHTHALMIC GEL FORMING SOLUTION)
TIMOPTIC-XE® 0.25% and 0.5%
(TIMOLOL MALEATE OPHTHALMIC GEL FORMING SOLUTION)

DESCRIPTION

TIMOPTIC-XE® (timolol maleate ophthalmic gel forming solution) is a non-selective beta-adrenergic receptor blocking agent. Its chemical name is (-)-1-(tert-butylamino)-3-[(4-morpholino-1,2,5-thiadiazol-3-yl)oxy]-2-propanol maleate (1:1) (salt). Timolol maleate possesses an asymmetric carbon atom in its structure and is provided as the levo-isomer. The optical rotation of timolol maleate is:

25°

[α] in 1.0N HCl (C = 5%) = -12.2° (-11.7° to -12.5°).

405 nm

Its molecular formula is C13H24N4O3S•C4H4O4 and its structural formula is:

Timolol maleate has a molecular weight of 432.49. It is a white, odorless, crystalline powder which is soluble in water; sparingly soluble in ethanol; slightly soluble in chloroform; practically insoluble in ether.

TIMOPTIC-XE Sterile Ophthalmic Gel Forming Solution is supplied as a sterile, isotonic, buffered, aqueous solution of timolol maleate in two dosage strengths. The pH of the solution is approximately 7.0, and the osmolarity is 260-330 mOsm. Each mL of TIMOPTIC-XE 0.25% contains 2.5 mg of timolol (3.4 mg of timolol maleate). Each mL of TIMOPTIC-XE 0.5% contains 5 mg of timolol (6.8 mg of timolol maleate). Inactive ingredients: gellan gum, tromethamine, mannitol, and water for injection. Preservative: benzododecinium bromide 0.012%.

The gel forming solution contains a purified anionic heteropolysaccharide derived from gellan gum. An aqueous solution of gellan gum, in the presence of a cation, has the ability to gel. Upon contact with the precorneal tear film, TIMOPTIC-XE forms a gel that is subsequently removed by the flow of tears.

CLINICAL PHARMACOLOGY

Mechanism of Action

Timolol maleate is a beta1 and beta2 (non-selective) adrenergic receptor blocking agent that does not have significant intrinsic sympathomimetic, direct myocardial depressant, or local anesthetic (membrane-stabilizing) activity.

TIMOPTIC-XE, when applied topically on the eye, has the action of reducing elevated, as well as normal intraocular pressure, whether or not accompanied by glaucoma. Elevated intraocular pressure is a major risk factor in the pathogenesis of glaucomatous visual field loss and optic nerve damage.

The precise mechanism of the ocular hypotensive action of TIMOPTIC-XE is not clearly established at this time. Tonography and fluorophotometry studies of TIMOPTIC® (timolol maleate ophthalmic solution) in man suggest that its predominant action may be related to reduced aqueous formation. However, in some studies, a slight increase in outflow facility was also observed.

Beta-adrenergic receptor blockade reduces cardiac output in both healthy subjects and patients with heart disease. In patients with severe impairment of myocardial function, beta-adrenergic receptor blockade may inhibit the stimulatory effect of the sympathetic nervous system necessary to maintain adequate cardiac function.

Beta-adrenergic receptor blockade in the bronchi and bronchioles results in increased airway resistance from unopposed parasympathetic activity. Such an effect in patients with asthma or other bronchospastic conditions is potentially dangerous.

Pharmacokinetics

In a study of plasma drug concentration in six subjects, the systemic exposure to timolol was determined following once daily administration of TIMOPTIC-XE 0.5% in the morning. The mean peak plasma concentration following this morning dose was 0.28 ng/mL.

Clinical Studies

In controlled, double-masked, multicenter clinical studies, comparing TIMOPTIC-XE 0.25% to TIMOPTIC 0.25% and TIMOPTIC-XE 0.5% to TIMOPTIC 0.5%, TIMOPTIC-XE administered once a day was shown to be equally effective in lowering intraocular pressure as the equivalent concentration of TIMOPTIC administered twice a day. The effect of timolol in lowering intraocular pressure was evident for 24 hours with a single dose of TIMOPTIC-XE. Repeated observations over a period of six months indicate that the intraocular pressure-lowering effect of TIMOPTIC-XE was consistent. The results from the largest U.S. and international clinical trials comparing TIMOPTIC-XE 0.5% to TIMOPTIC 0.5% are shown in Figure 1.

Figure 1
Mean IOP and Std Deviation
(mm Hg) by Treatment Group

TIMOPTIC-XE administered once daily had a safety profile similar to that of an equivalent concentration of TIMOPTIC administered twice daily. Due to the physical characteristics of the formulation, there was a higher incidence of transient blurred vision in patients administered TIMOPTIC-XE. A slight reduction in resting heart rate was observed in some patients receiving TIMOPTIC-XE 0.5% (mean reduction 24 hours post-dose 0.8 beats/minute, mean reduction 2 hours post-dose 3.8 beats/minute) [see ADVERSE REACTIONS].

TIMOPTIC-XE has not been studied in patients wearing contact lenses.

INDICATIONS AND USAGE

TIMOPTIC-XE Sterile Ophthalmic Gel Forming Solution is indicated in the treatment of elevated intraocular pressure in patients with ocular hypertension or open-angle glaucoma.

CONTRAINDICATIONS

TIMOPTIC-XE is contraindicated in patients with (1) bronchial asthma; (2) a history of bronchial asthma; (3) severe chronic obstructive pulmonary disease [see WARNINGS, Obstructive Pulmonary Disease]; (4) sinus bradycardia; (5) second or third degree atrioventricular block; (6) overt cardiac failure [see WARNINGS, Cardiac Failure]; (7) cardiogenic shock; or (8) hypersensitivity to any component of this product.

WARNINGS

As with many topically applied ophthalmic drugs, this drug is absorbed systemically.

The same adverse reactions found with systemic administration of beta-adrenergic blocking agents may occur with topical ophthalmic administration. For example, severe respiratory reactions and cardiac reactions, including death due to bronchospasm in patients with asthma, and rarely death in association with cardiac failure, have been reported following systemic or ophthalmic administration of timolol maleate [see CONTRAINDICATIONS].

Cardiac Failure

Sympathetic stimulation may be essential for support of the circulation in individuals with diminished myocardial contractility, and its inhibition by beta-adrenergic receptor blockade may precipitate more severe failure.

In Patients Without a History of Cardiac Failure continued depression of the myocardium with beta-blocking agents over a period of time can, in some cases, lead to cardiac failure. At the first sign or symptom of cardiac failure, TIMOPTIC-XE should be discontinued.

Obstructive Pulmonary Disease

Patients with chronic obstructive pulmonary disease (e.g., chronic bronchitis, emphysema) of mild or moderate severity, bronchospastic disease, or a history of bronchospastic disease (other than bronchial asthma or a history of bronchial asthma) in which TIMOPTIC-XE is contraindicated [see CONTRAINDICATIONS] should, in general, not receive beta-blockers, including TIMOPTIC-XE.

Major Surgery

The necessity or desirability of withdrawal of beta-adrenergic blocking agents prior to major surgery is controversial. Beta-adrenergic receptor blockade impairs the ability of the heart to respond to beta-adrenergically mediated reflex stimuli. This may augment the risk of general anesthesia in surgical procedures. Some patients receiving beta-adrenergic receptor blocking agents have experienced protracted, severe hypotension during anesthesia. Difficulty in restarting and maintaining the heartbeat has also been reported. For these reasons, in patients undergoing elective surgery, some authorities recommend gradual withdrawal of beta-adrenergic receptor blocking agents.

If necessary during surgery, the effects of beta-adrenergic blocking agents may be reversed by sufficient doses of adrenergic agonists.

Diabetes Mellitus

Beta-adrenergic blocking agents should be administered with caution in patients subject to spontaneous hypoglycemia or to diabetic patients (especially those with labile diabetes) who are receiving insulin or oral hypoglycemic agents. Beta-adrenergic receptor blocking agents may mask the signs and symptoms of acute hypoglycemia.

Thyrotoxicosis

Beta-adrenergic blocking agents may mask certain clinical signs (e.g., tachycardia) of hyperthyroidism. Patients suspected of developing thyrotoxicosis should be managed carefully to avoid abrupt withdrawal of beta-adrenergic blocking agents that might precipitate a thyroid storm.

PRECAUTIONS

General

Because of potential effects of beta-adrenergic blocking agents on blood pressure and pulse, these agents should be used with caution in patients with cerebrovascular insufficiency. If signs or symptoms suggesting reduced cerebral blood flow develop following initiation of therapy with TIMOPTIC-XE, alternative therapy should be considered.

There have been reports of bacterial keratitis associated with the use of multiple-dose containers of topical ophthalmic products. These containers had been inadvertently contaminated by patients who, in most cases, had a concurrent corneal disease or a disruption of the ocular epithelial surface [see PRECAUTIONS, Information for Patients].

Choroidal detachment after filtration procedures has been reported with the administration of aqueous suppressant therapy (e.g., timolol).

Angle-Closure Glaucoma

In patients with angle-closure glaucoma, the immediate objective of treatment is to reopen the angle. This may require constricting the pupil. Timolol maleate has little or no effect on the pupil. TIMOPTIC‑XE should not be used alone in the treatment of angle-closure glaucoma.

Anaphylaxis

While taking beta-blockers, patients with a history of atopy or a history of severe anaphylactic reactions to a variety of allergens may be more reactive to repeated accidental, diagnostic, or therapeutic challenge with such allergens. Such patients may be unresponsive to the usual doses of epinephrine used to treat anaphylactic reactions.

Muscle Weakness

Beta-adrenergic blockade has been reported to potentiate muscle weakness consistent with certain myasthenic symptoms (e.g., diplopia, ptosis, and generalized weakness). Timolol has been reported rarely to increase muscle weakness in some patients with myasthenia gravis or myasthenic symptoms.

Information for Patients

Patients should be instructed to avoid allowing the tip of the dispensing container to contact the eye or surrounding structures.

Patients should also be instructed that ocular solutions, if handled improperly or if the tip of the dispensing container contacts the eye or surrounding structures, can become contaminated by common bacteria known to cause ocular infections. Serious damage to the eye and subsequent loss of vision may result from using contaminated solutions [see PRECAUTIONS, General].

Patients should also be advised that if they have ocular surgery or develop an intercurrent ocular condition (e.g., trauma or infection), they should immediately seek their physician’s advice concerning the continued use of the present multidose container.

Patients should be instructed to invert the closed container and shake once before each use. It is not necessary to shake the container more than once.

Patients requiring concomitant topical ophthalmic medications should be instructed to administer these at least 10 minutes before instilling TIMOPTIC-XE.

Patients with bronchial asthma, a history of bronchial asthma, severe chronic obstructive pulmonary disease, sinus bradycardia, second or third degree atrioventricular block, or cardiac failure should be advised not to take this product [see CONTRAINDICATIONS].

Transient blurred vision, generally lasting from 30 seconds to 5 minutes, following instillation, and potential visual disturbances may impair the ability to perform hazardous tasks such as operating machinery or driving a motor vehicle.

Drug Interactions

Beta-Adrenergic Blocking Agents

Patients who are receiving a beta-adrenergic blocking agent orally and TIMOPTIC-XE should be observed for potential additive effects of beta-blockade, both systemic and on intraocular pressure. The concomitant use of two topical beta-adrenergic blocking agents is not recommended.

Calcium Antagonists

Caution should be used in the coadministration of beta-adrenergic blocking agents, such as TIMOPTIC‑XE, and oral or intravenous calcium antagonists because of possible atrioventricular conduction disturbances, left ventricular failure, or hypotension. In patients with impaired cardiac function, coadministration should be avoided.

Catecholamine-Depleting Drugs

Close observation of the patient is recommended when a beta-blocker is administered to patients receiving catecholamine-depleting drugs such as reserpine, because of possible additive effects and the production of hypotension and/or marked bradycardia, which may result in vertigo, syncope, or postural hypotension.

Digitalis and Calcium Antagonists

The concomitant use of beta-adrenergic blocking agents with digitalis and calcium antagonists may have additive effects in prolonging atrioventricular conduction time.

CYP2D6 Inhibitors

Potentiated systemic beta-blockade (e.g., decreased heart rate, depression) has been reported during combined treatment with CYP2D6 inhibitors (e.g., quinidine, SSRIs) and timolol.

Clonidine

Oral beta-adrenergic blocking agents may exacerbate the rebound hypertension which can follow the withdrawal of clonidine. There have been no reports of exacerbation of rebound hypertension with ophthalmic timolol maleate.

Injectable Epinephrine

[See PRECAUTIONS, General, Anaphylaxis]

Carcinogenesis, Mutagenesis, Impairment of Fertility

In a two-year study of timolol maleate administered orally to rats, there was a statistically significant increase in the incidence of adrenal pheochromocytomas in male rats administered 300 mg/kg/day (approximately 42,000 times the systemic exposure following the maximum recommended human ophthalmic dose). Similar differences were not observed in rats administered oral doses equivalent to approximately 14,000 times the maximum recommended human ophthalmic dose.

In a lifetime oral study in mice, there were statistically significant increases in the incidence of benign and malignant pulmonary tumors, benign uterine polyps, and mammary adenocarcinomas in female mice at 500 mg/kg/day (approximately 71,000 times the systemic exposure following the maximum recommended human ophthalmic dose), but not at 5 or 50 mg/kg/day (approximately 700 or 7,000, respectively, times the systemic exposure following the maximum recommended human ophthalmic dose). In a subsequent study in female mice, in which post-mortem examinations were limited to the uterus and the lungs, a statistically significant increase in the incidence of pulmonary tumors was again observed at 500 mg/kg/day.

The increased occurrence of mammary adenocarcinomas was associated with elevations in serum prolactin, which occurred in female mice administered oral timolol at 500 mg/kg/day, but not at oral doses of 5 or 50 mg/kg/day. An increased incidence of mammary adenocarcinomas in rodents has been associated with administration of several other therapeutic agents that elevate serum prolactin, but no correlation between serum prolactin levels and mammary tumors has been established in humans. Furthermore, in adult human female subjects who received oral dosages of up to 60 mg of timolol maleate (the maximum recommended human oral dosage), there were no clinically meaningful changes in serum prolactin.

Timolol maleate was devoid of mutagenic potential when tested in vivo (mouse) in the micronucleus test and cytogenetic assay (doses up to 800 mg) and in vitro in a neoplastic cell transformation assay (up to 100 mcg/mL). In Ames tests, the highest concentrations of timolol employed, 5,000 or 10,000 mcg/plate, were associated with statistically significant elevations of revertants observed with tester strain TA 100 (in seven replicate assays), but not in the remaining three strains. In the assays with tester strain TA 100, no consistent dose-response relationship was observed, and the ratio of test to control revertants did not reach 2. A ratio of 2 is usually considered the criterion for a positive Ames test.

Reproduction and fertility studies in rats demonstrated no adverse effect on male or female fertility at doses up to 21,000 times the systemic exposure following the maximum recommended human ophthalmic dose.

Pregnancy

Teratogenic Effects

Teratogenicity studies with timolol in mice, rats, and rabbits at oral doses up to 50 mg/kg/day (7,000 times the systemic exposure following the maximum recommended human ophthalmic dose) demonstrated no evidence of fetal malformations. Although delayed fetal ossification was observed at this dose in rats, there were no adverse effects on postnatal development of offspring. Doses of 1,000 mg/kg/day (142,000 times the systemic exposure following the maximum recommended human ophthalmic dose) were maternotoxic in mice and resulted in an increased number of fetal resorptions. Increased fetal resorptions were also seen in rabbits at doses of 14,000 times the systemic exposure following the maximum recommended human ophthalmic dose, in this case without apparent maternotoxicity.

There are no adequate and well-controlled studies in pregnant women. TIMOPTIC-XE should be used during pregnancy only if the potential benefit justifies the potential risk to the fetus.

Nursing Mothers

Timolol maleate has been detected in human milk following oral and ophthalmic drug administration. Because of the potential for serious adverse reactions from TIMOPTIC-XE in nursing infants, a decision should be made whether to discontinue nursing or to discontinue the drug, taking into account the importance of the drug to the mother.

Pediatric Use

Safety and effectiveness of timolol maleate ophthalmic solution have been established when administered in pediatric patients aged 2 years and older. Use of timolol maleate ophthalmic solution in these children is supported by evidence from adequate and well-controlled studies in children and adults. Safety and efficacy in pediatric patients below the age of 2 years have not been established.

Geriatric Use

No overall differences in safety or effectiveness have been observed between elderly and younger patients.

ADVERSE REACTIONS

In clinical trials, transient blurred vision upon instillation of the drop was reported in approximately one in three patients (lasting from 30 seconds to 5 minutes). Less than 1% of patients discontinued from the studies due to blurred vision.

The frequency of patients reporting burning and stinging upon instillation was comparable between TIMOPTIC-XE and TIMOPTIC (approximately one in eight patients).

Adverse experiences reported in 1-5% of patients were:

Ocular: | Pain, conjunctivitis, discharge (e.g., crusting), foreign body sensation, itching and tearing;
Systemic: | Headache, dizziness, and upper respiratory infections.

The following additional adverse experiences have been reported with the ocular administration of this or other timolol maleate formulations:

BODY AS A WHOLE

Asthenia/fatigue, and chest pain.

CARDIOVASCULAR

Bradycardia, arrhythmia, hypotension, hypertension, syncope, heart block, cerebrovascular accident, cerebral ischemia, cardiac failure, worsening of angina pectoris, palpitation, cardiac arrest, pulmonary edema, edema, claudication, Raynaud’s phenomenon, and cold hands and feet.

DIGESTIVE

Nausea, diarrhea, dyspepsia, anorexia, and dry mouth.

IMMUNOLOGIC

Systemic lupus erythematosus.

NERVOUS SYSTEM/PSYCHIATRIC

Increase in signs and symptoms of myasthenia gravis, paresthesia, somnolence, insomnia, nightmares, behavioral changes and psychic disturbances including depression, confusion, hallucinations, anxiety, disorientation, nervousness, and memory loss.

SKIN

Alopecia and psoriasiform rash or exacerbation of psoriasis.

HYPERSENSITIVITY

Signs and symptoms of systemic allergic reactions including anaphylaxis, angioedema, urticaria, localized and generalized rash.

RESPIRATORY

Bronchospasm (predominantly in patients with preexisting bronchospastic disease), respiratory failure, dyspnea, nasal congestion, cough and upper respiratory infections.

ENDOCRINE

Masked symptoms of hypoglycemia in diabetic patients [see WARNINGS, Diabetes Mellitus].

SPECIAL SENSES

Signs and symptoms of ocular irritation including blepharitis, keratitis, and dry eyes; ptosis; decreased corneal sensitivity; cystoid macular edema; visual disturbances including refractive changes and diplopia; pseudopemphigoid; choroidal detachment following filtration surgery [see PRECAUTIONS, General]; and tinnitus.

UROGENITAL

Retroperitoneal fibrosis, decreased libido, impotence, and Peyronie’s disease.

The following additional adverse effects have been reported in clinical experience with ORAL timolol maleate or other ORAL beta-blocking agents and may be considered potential effects of ophthalmic timolol maleate: Allergic: Erythematous rash, fever combined with aching and sore throat, laryngospasm with respiratory distress; Body as a Whole: Extremity pain, decreased exercise tolerance, weight loss; Cardiovascular: Worsening of arterial insufficiency, vasodilatation; Digestive: Gastrointestinal pain, hepatomegaly, vomiting, mesenteric arterial thrombosis, ischemic colitis; Hematologic: Nonthrombocytopenic purpura, thrombocytopenic purpura, agranulocytosis; Endocrine: Hyperglycemia, hypoglycemia; Skin: Pruritus, skin irritation, increased pigmentation, sweating; Musculoskeletal: Arthralgia; Nervous System/Psychiatric: Vertigo, local weakness, diminished concentration, reversible mental depression progressing to catatonia, an acute reversible syndrome characterized by disorientation for time and place, emotional lability, slightly clouded sensorium, and decreased performance on neuropsychometrics; Respiratory: Rales, bronchial obstruction; Urogenital: Urination difficulties.

To report SUSPECTED ADVERSE REACTIONS, contact Bausch & Lomb Incorporated at 1-800-553-5340 or FDA at 1-800-FDA-1088 or www.fda.gov/medwatch.

OVERDOSAGE

No data are available in regard to human overdosage with or accidental oral ingestion of TIMOPTIC‑XE.

There have been reports of inadvertent overdosage with TIMOPTIC Ophthalmic Solution resulting in systemic effects similar to those seen with systemic beta-adrenergic blocking agents such as dizziness, headache, shortness of breath, bradycardia, bronchospasm, and cardiac arrest [see ADVERSE REACTIONS].

Overdosage has been reported with timolol maleate tablets. A 30-year-old female ingested 650 mg of timolol maleate tablets (maximum recommended oral daily dose is 60 mg) and experienced second and third degree heart block. She recovered without treatment but approximately two months later developed irregular heartbeat, hypertension, dizziness, tinnitus, faintness, increased pulse rate, and borderline first degree heart block.

An in vitro hemodialysis study, using ^14C timolol added to human plasma or whole blood, showed that timolol was readily dialyzed from these fluids; however, a study of patients with renal failure showed that timolol did not dialyze readily.

DOSAGE AND ADMINISTRATION

Patients should be instructed to invert the closed container and shake once before each use. It is not necessary to shake the container more than once. Other topically applied ophthalmic medications should be administered at least 10 minutes before TIMOPTIC-XE [see PRECAUTIONS, Information for Patients and accompanying INSTRUCTIONS FOR USE].

TIMOPTIC-XE Sterile Ophthalmic Gel Forming Solution is available in concentrations of 0.25% and 0.5%. The dose is one drop of TIMOPTIC-XE (either 0.25% or 0.5%) in the affected eye(s) once a day.

Because in some patients the pressure-lowering response to TIMOPTIC-XE may require a few weeks to stabilize, evaluation should include a determination of intraocular pressure after approximately 4 weeks of treatment with TIMOPTIC-XE.

Dosages higher than one drop of 0.5% TIMOPTIC-XE once a day have not been studied. If the patient’s intraocular pressure is still not at a satisfactory level on this regimen, concomitant therapy can be considered. The concomitant use of two topical beta-adrenergic blocking agents is not recommended [see PRECAUTIONS, Drug Interactions, Beta-Adrenergic Blocking Agents].

When patients have been switched from therapy with TIMOPTIC administered twice daily to TIMOPTIC-XE administered once daily, the ocular hypotensive effect has remained consistent.

HOW SUPPLIED

TIMOPTIC-XE (timolol maleate ophthalmic gel forming solution) is a colorless to nearly colorless, slightly opalescent, and slightly viscous solution.

TIMOPTIC-XE (timolol maleate ophthalmic gel forming solution), 0.25% timolol equivalent, is supplied in a white low density polyethylene (LDPE) dispenser with a controlled drop tip and a yellow polypropylene cap as follows:

NDC 24208-814-25, 5 mL in a 7.5 mL capacity bottle.

TIMOPTIC-XE (timolol maleate ophthalmic gel forming solution), 0.5% timolol equivalent, is supplied in a white low density polyethylene (LDPE) dispenser with a controlled drop tip and a yellow polypropylene cap as follows:

NDC 24208-816-05, 5 mL in a 7.5 mL capacity bottle.

Storage
Store at 15°C to 25°C (59°F to 77°F). Avoid freezing. Protect from light.

Distributed by:

Bausch & Lomb Americas Inc.

Bridgewater, NJ 08807 USA

Manufactured by:

Bausch & Lomb Incorporated

Tampa, FL 33637 USA

TIMOPTIC and TIMOPTIC-XE are trademarks of Bausch & Lomb Incorporated or its affiliates.

© 2022 Bausch & Lomb Incorporated or its affiliates

Revised: 03/2022

9752801

STERILE OPHTHALMIC GEL FORMING SOLUTION TIMOPTIC-XE® 0.25% AND 0.5% (TIMOLOL MALEATE OPHTHALMIC GEL FORMING SOLUTION) Instructions for Use

TIMOPTIC-XE® (tim-op´tik-XE)

(timolol maleate ophthalmic gel forming solution) 0.25% and 0.5%

Read this Instructions for Use that comes with TIMOPTIC-XE before you start using it and each time you get a refill. There may be new information. This information does not take the place of talking with your doctor about your medical condition or treatment.

Important information about TIMOPTIC-XE:

- Use TIMOPTIC-XE exactly as your doctor tells you to use it. Your doctor will tell you how much TIMOPTIC-XE to use and when to use it.
- If you use other medicines in your eye, wait at least 10 minutes between using TIMOPTIC-XE and your other eye medicines.
- Do not touch your eye or areas around your eye with the tip of the TIMOPTIC-XE bottle. You may get bacteria on the tip of the bottle that can cause you to get an eye infection that can lead to serious eye damage or vision loss.

How should I use TIMOPTIC-XE?

Step 1. Wash your hands.

Step 2. Turn your closed bottle of TIMOPTIC-XE upside down (invert) and shake once.

Step 3. Remove the TIMOPTIC-XE cap by turning the cap in the direction of the arrows shown (See Figure A). Put the cap in a clean and dry area. Do not let the tip of the bottle touch your fingers or other surfaces.

Figure A

Step 4. Hold the bottle between your thumb and index finger with 1 hand. Use the index finger of the other hand to pull down the lower eyelid to form a pocket for the eye drop (See Figure B). Tilt your head backwards.

Figure B

Step 5. Place the tip of the bottle close to your eye. Be careful not to touch your eye with the tip of the bottle. Gently squeeze the bottle and let 1 drop fall into the space between your lower eyelid and your eye (See Figure C). If a drop misses your eye, follow the instructions in steps 4 and 5 again.

Figure C

Step 6. If your doctor has told you to use TIMOPTIC-XE in both eyes, repeat steps 4 and 5 for your other eye.

Step 7. Put the cap back on the bottle and close.

- The TIMOPTIC-XE bottle tip is made to give 1 drop at a time. Do not try to make the hole in the tip of your bottle bigger.
- Do not wash the bottle tip.
- After you have used all of your TIMOPTIC-XE doses, there will be some TIMOPTIC-XE left in the bottle. Do not try to remove the extra TIMOPTIC-XE from the bottle. Throw it away.

How should I store TIMOPTIC-XE?

- Store TIMOPTIC-XE at room temperature between 59°F to 77°F (15°C to 25°C) in an upright position.
- Do not freeze TIMOPTIC-XE.
- Keep TIMOPTIC-XE out of light.

Keep TIMOPTIC-XE and all medicines out of the reach of children.

If you would like more information, talk with your doctor. You can ask your pharmacist or doctor for more information about TIMOPTIC-XE that is written for health professionals.

This Instructions for Use has been approved by the U.S. Food and Drug Administration.

Distributed by:
Bausch & Lomb Americas Inc.

Bridgewater, NJ 08807 USA

Manufactured by:
Bausch & Lomb Incorporated
Tampa, FL 33637 USA

TIMOPTIC and TIMOPTIC-XE are trademarks of Bausch & Lomb Incorporated or its affiliates.

© 2022 Bausch & Lomb Incorporated or its affiliates

Revised: 03/2022

9752801

Package/Label Display Pane– 0.25% Carton

NDC 24208-814-25

STERILE

TIMOPTIC-XE®
(Timolol Maleate
Ophthalmic Gel
Forming Solution)
0.25%

Timolol Equivalent
(Timolol Maleate 3.4 mg/mL
equivalent to 2.5 mg/mL timolol)

FOR TOPICAL APPLICATION
IN THE EYE
Rx only
5 mL
BAUSCH + LOMB
9752501
AB44007

Package/Label Display Pane – 0.5% Carton

NDC 24208-816-05

STERILE

TIMOPTIC-XE®
(Timolol Maleate
Ophthalmic Gel
Forming Solution)
0.5%

Timolol Equivalent
(Timolol Maleate 6.8 mg/mL
equivalent to 5 mg/mL timolol)

FOR TOPICAL APPLICATION
IN THE EYE

Rx only
5 mL
BAUSCH + LOMB

9752701
AB44107